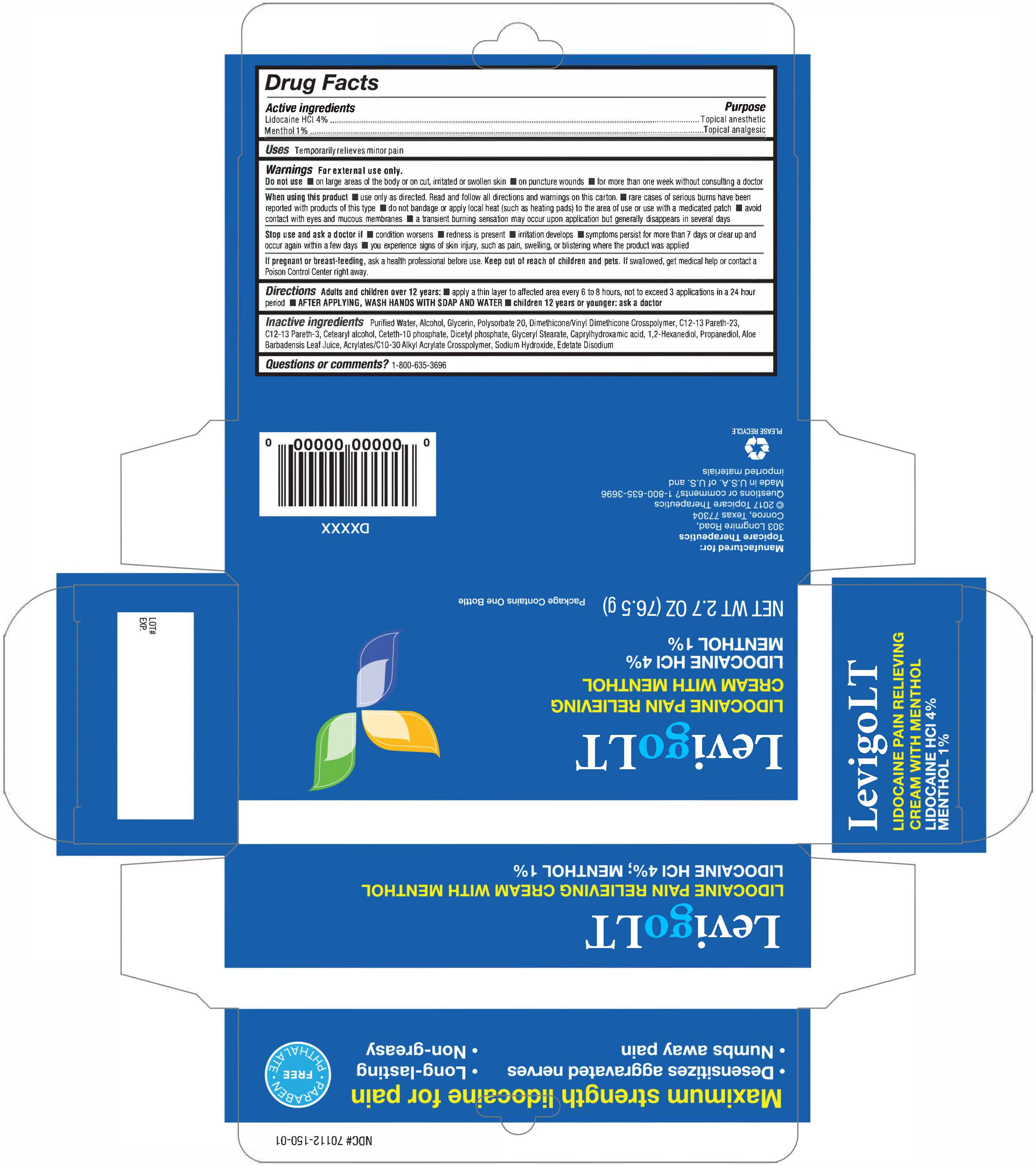 DRUG LABEL: LevigoLT
NDC: 70112-150 | Form: CREAM
Manufacturer: Topicare Management, LLC
Category: otc | Type: HUMAN OTC DRUG LABEL
Date: 20170525

ACTIVE INGREDIENTS: LIDOCAINE HYDROCHLORIDE 4 g/100 g; MENTHOL 1 g/100 g
INACTIVE INGREDIENTS: ALCOHOL; POLYSORBATE 20; SODIUM HYDROXIDE; WATER; CETETH-10 PHOSPHATE; EDETATE DISODIUM; DIHEXADECYL PHOSPHATE; ALOE VERA LEAF; CARBOMER INTERPOLYMER TYPE A (ALLYL SUCROSE CROSSLINKED); GLYCERYL MONOSTEARATE; 1,2-HEXANEDIOL; DIMETHICONE/VINYL DIMETHICONE CROSSPOLYMER (SOFT PARTICLE); GLYCERIN; C12-13 PARETH-23; PROPANEDIOL; CAPRYLHYDROXAMIC ACID; C12-13 PARETH-3; CETOSTEARYL ALCOHOL

Description

LevigoLT is a Lidocaine HCI 4% and Menthol 1% topical anesthetic and analgesic cream indicated to temporarily relieve minor pain.

Active Ingredients

Each gram of LevigoLT contains:

Lidocaine HCI 4% (40mg) Topical Anesthetic

Menthol 1% (10mg) Topical Analgesic

Purpose

Temporarily relieves minor pain associated with: arthritis, simple backache, sprains, bruises, muscles soreness, cramps

Warnings

For external use only. Do not use on large areas of the body or on cut, irritated or swollen skin, puncture wounds, or for more than one week without consulting a doctor.

When using this product use only as directed. Read and follow all directions and warnings on this carton. *was hands with soap and water after applying *rare cases of serious burns have been reported with product of this type *do not bandage or apply local heat (such as heating pads) to the area of use or use with a medicated patch *avoid contact with eyes and mucous membranes *atransient burning sensation may occur upon application but generally disappears in several days

Ask Doctor

Stop use and ask a doctor if *condition worsens *redness is present * irritation develops *symptoms persist more than 7 days or clear up and occur again within a few days *you experience signs of skin injury, such as pain, swelling, or blistering where the product was applied.

Pregnancy or Breast Feeding

If pregnant or breast feeding, ask a health professional before use.

Keep out of reach of children and pets. If swallowed, get medical help or contact a Poinson Control Center right away.

Indications & Usage

Directions: Adults and children over 12 year: *apply a thin layer to affected area every 6 to 8 hours, not to exceed 3 applications in a 24-hour period *after applying, wash hands with soap and water *children 12 years or younger: ask a doctor.

Questions or Comments

For questions or comments, call 1-800-635-3696.

Dosage and Administration

Distributed by: Topicare Therapeutics, LLC. 1925 Longmire Rd. Building 2, Conroe, TX 77304

Made in U.S.A. of U.S. and imported materials

Inactive Ingredients

Purified Water, Alcohol, Glycerin, Polysorbate 20, Dimethicone/Vinyl Dimethicone Crosspolymer, C12-13 Pareth-23, C12-13 Pareth-3, Cetearyl alcohol, Ceteth-10 phosphate, Dicetyl phosphate, Glyceryl Stearate, Caprylhydroxamic acid, 1,2-Hexanediol, Propanediol, Aloe Barbadensis Leaf Juice, Acrylates/C10-30 Alkyl Acrylate Crosspolymer, Sodium Hydroxide, Edetate Disodium

Storage and Handling

Store at 25°C (77°F); excursions permitted to 15°-30°C (59°-86°F). Protect from freezing.